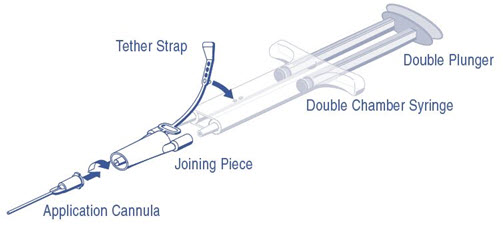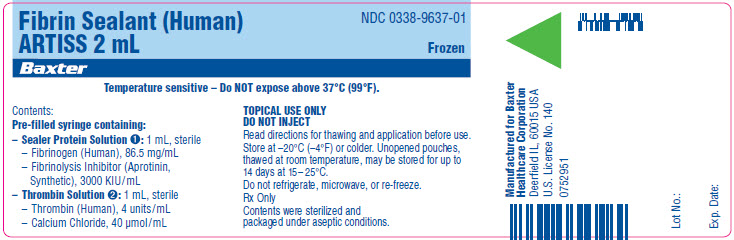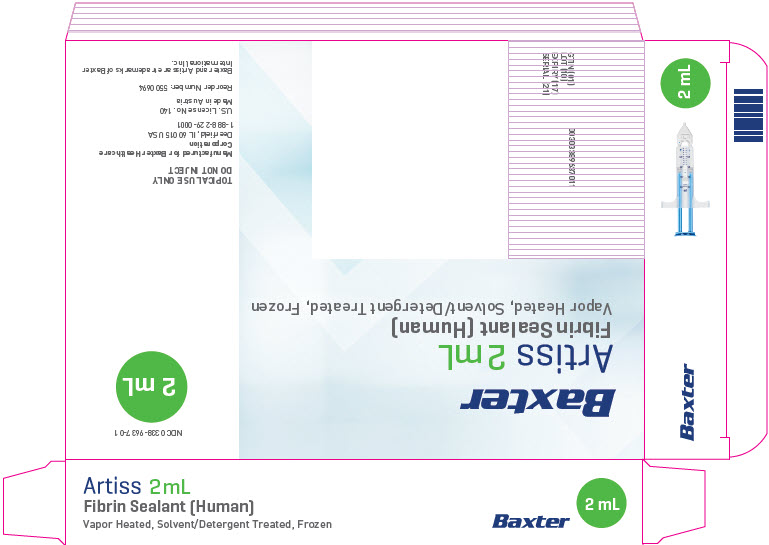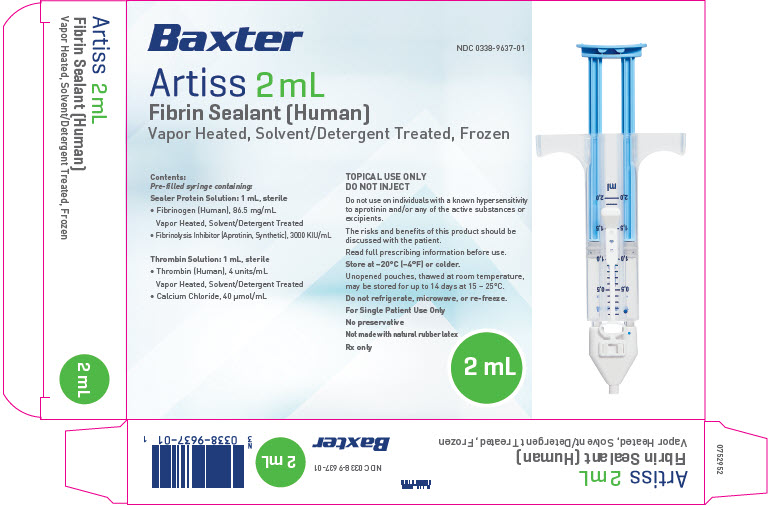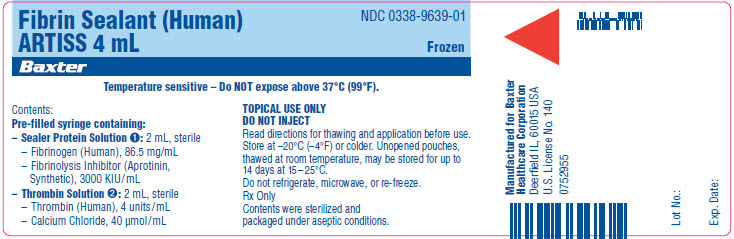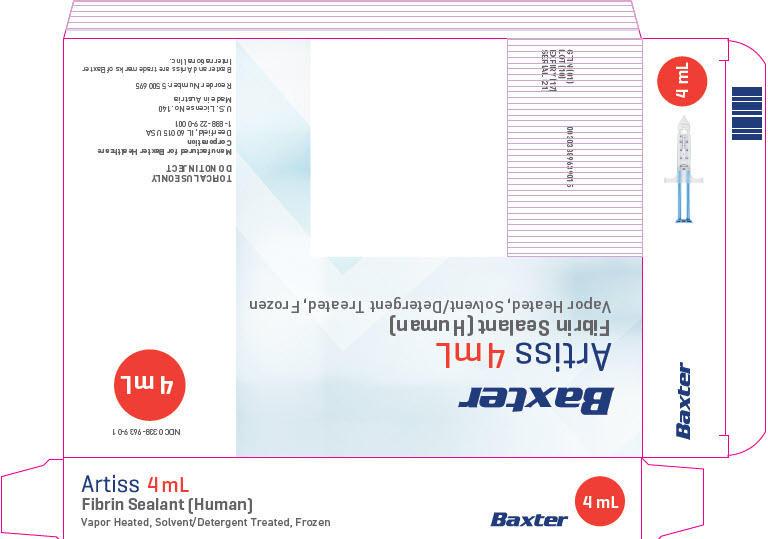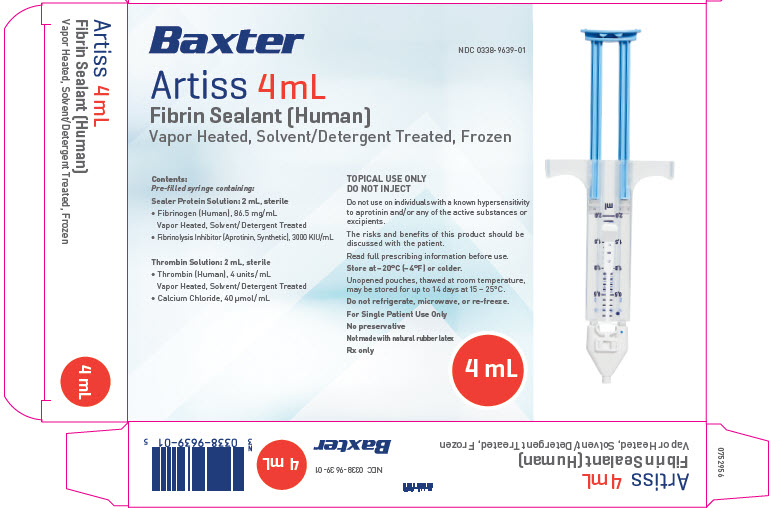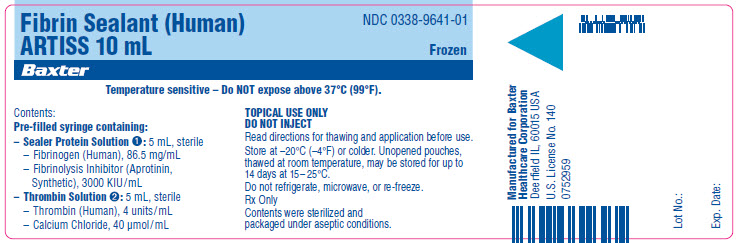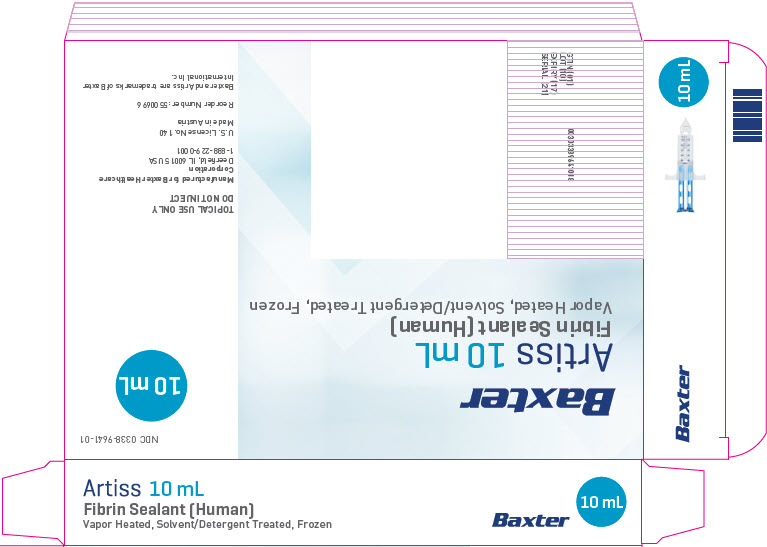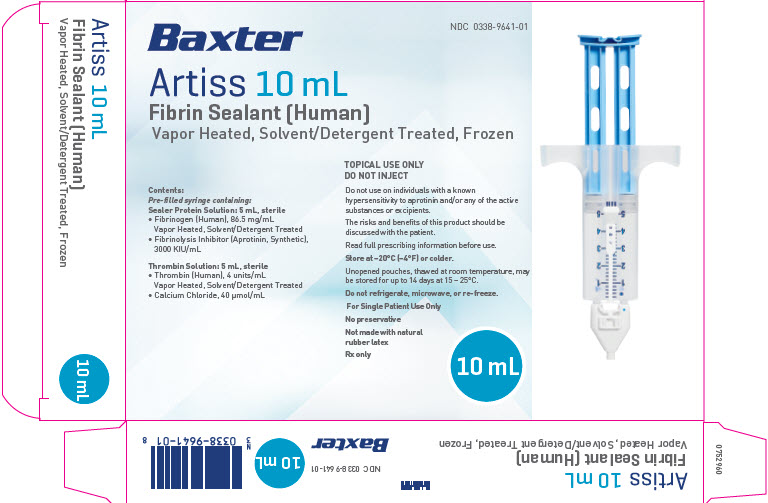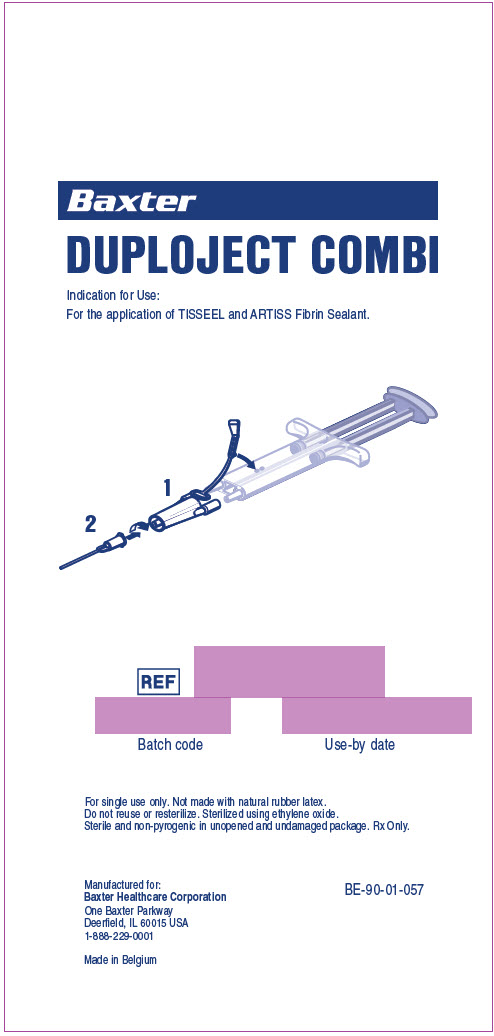 DRUG LABEL: ARTISS
NDC: 0338-8503 | Form: SOLUTION
Manufacturer: Baxter Healthcare Corporation
Category: other | Type: PLASMA DERIVATIVE
Date: 20250930

ACTIVE INGREDIENTS: FIBRINOGEN HUMAN 86.5 mg/1 mL; HUMAN THROMBIN 4 [iU]/1 mL
INACTIVE INGREDIENTS: APROTININ; CALCIUM CHLORIDE; ALBUMIN HUMAN; TRISODIUM CITRATE DIHYDRATE; HISTIDINE; NIACINAMIDE; POLYSORBATE 80; SODIUM CHLORIDE; WATER

HIGHLIGHTS OF PRESCRIBING INFORMATION

These highlights do not include all the information needed to use ARTISS safely and effectively. See full prescribing information for ARTISS.
ARTISS [Fibrin Sealant (Human)] Frozen Solution for topical application
Initial U.S. Approval: 2008

RECENT MAJOR CHANGES

Indications and Usage (1) 09/2025
Dosage and Administration (2.1, 2.2, 2.3) 09/2025

1 INDICATIONS AND USAGE

ARTISS is a fibrin sealant indicated in adult and pediatric patients to:

- Adhere autologous skin grafts to surgically prepared wound beds resulting from burns. (1)
- Adhere tissue flaps during facial rhytidectomy surgery. (1)

Limitations of Use
ARTISS is not indicated as an adjunct to hemostasis. (1)

2 DOSAGE AND ADMINISTRATION

For topical use only. (2.1)
Individualize the amount based on the size of the surface to be covered. (2.1)

- 2 mL will cover approximately 100 cm^2 surface area
- 4 mL will cover approximately 200 cm^2 surface area
- 10 mL will cover approximately 500 cm^2 surface area

Apply a thin layer using the EASYSPRAY and Spray Set or Duploject Combi or an equivalent device cleared by FDA for application of ARTISS. (2.3)

3 DOSAGE FORMS AND STRENGTHS

ARTISS solution is available as a 2 mL, 4 mL, and 10 mL (total volume) pre-filled syringe with the DUPLOJECT COMBI. (3)

4 CONTRAINDICATIONS

- Do not inject directly into the circulatory system. (4)
- Do not use in individuals with a known hypersensitivity to aprotinin. (4)
- Do not spray where the minimum recommended distance from the applicator tip to the target site cannot be assured. (4)

5 WARNINGS AND PRECAUTIONS

- Hypersensitivity reactions, including anaphylaxis: Should symptoms occur, discontinue and administer appropriate treatment. (5.1)
- Air or Gas Embolism: To reduce the risk of potential life-threatening gas embolism, spray using only the appropriate pressurized gas at the recommended pressure (21.8-29.0 psi) and distance (10-15 cm). Use the EASYSPRAY device connected to a Medical grade CO2, Compressed Air or Nitrogen. (5.2)
- Protein Denaturation: ARTISS may denature when exposed to solutions containing alcohol, iodine or heavy metals. (5.3)
- Transmission of Infectious Agents: As ARTISS is made from human plasma, it may carry the risk of transmitting infectious agents, e.g., viruses, the variant Creutzfeldt-Jakob disease (vCJD) and theoretically, the classic Creutzfeldt-Jakob disease agent. (5.4)

6 ADVERSE REACTIONS

Most common adverse reactions (incidence ≥1%) were:
Burns: Skin graft failure, hematoma and pruritus. (6.1)
Facial Rhytidectomy: Hematoma/seroma. (6.1)

To report SUSPECTED ADVERSE REACTIONS, contact Baxter Healthcare Corporation at 1-888-229-0001 or FDA at 1-800-FDA-1088 or www.fda.gov/medwatch.

FULL PRESCRIBING INFORMATION

1 INDICATIONS AND USAGE

ARTISS is a fibrin sealant indicated in adult and pediatric patients to:

- Adhere autologous skin grafts to surgically prepared wound beds resulting from burns.
- Adhere tissue flaps during facial rhytidectomy surgery.

Limitations of Use
ARTISS is not indicated as an adjunct to hemostasis.

2 DOSAGE AND ADMINISTRATION

Click here to enter Dosage and Administration

2.1 Recommended Dosage

For topical use only.

The recommended dosage of ARTISS is based on the surface area of the wound to be covered.

The approximate surface areas covered by each package size are listed in Table 1 below:

Table 1: Surface Area Coverage
Approximate area requiring skin graft fixation | Required package size of ARTISS
100 cm^2 | 2 mL
200 cm^2 | 4 mL
500 cm^2 | 10 mL

2.2 Preparation

Do not expose to temperatures above 37°C.
Do not microwave.
Do not refrigerate or re-freeze after thawing.
Do not use ARTISS unless it is completely thawed and warmed to 33°C-37°C.
Remove the protective syringe cap only after thawing is complete and the application tip is ready to be attached.
To facilitate removal of the tip cap from the syringe, rock the tip cap by moving it backward and forward, then pull the protective cap off the syringe.

Thaw and warm pre-filled syringes using one of the following options:

Quick Thawing /Warming Methods:

An overview of the quick thawing/warming methods is provided in Table 2.

Table 2: Quick Thawing/Warming Methods at 33°C-37°C (Minimum Thawing/Warming Times)
Pack Size | Sterile Water Bath (Pouches Removed) | Non-Sterile Water Bath (In Pouches) | Incubator (In Pouches)
2 mL | 5 minutes | 15 minutes | 40 minutes
4 mL | 5 minutes | 20 minutes | 50 minutes
10 mL | 10 minutes | 35 minutes | 90 minutes

Sterile Water Bath (Recommended Method): Transfer inner pouch to the sterile field, remove pre-filled syringe from inner pouch and place directly into sterile water bath ensuring the syringe is completely immersed in the water. (See Table 2 for minimum thawing/warming times). Maintain the product at 33°C to 37°C until use. To monitor the specified temperature range, control the water temperature using a thermometer and change the water as necessary. Once the package is opened or the product is warmed to 33°C to 37°C, it must be used within 12 hours.

Non-Sterile Water Bath: Maintain the pre-filled syringe in pouches and place into a water bath outside the sterile field ensuring the pouches remain submerged. (See Table 2 for minimum thawing/warming times). Remove from the water bath after thawing and warming, dry the external pouch and transfer inner pouch with pre-filled syringe onto the sterile field. Maintain the product at 33°C to 37°C until use. Once the package is opened or the product is warmed to 33°C to 37°C, it must be used within 12 hours.

Incubator: Maintain the pre-filled syringe in pouches and place into an incubator outside the sterile field. (See Table 2 for minimum thawing/warming times). Remove from the incubator after thawing and warming. Transfer inner pouch with pre-filled syringe onto the sterile field. Maintain the product at 33°C to 37°C until use. Once the package is opened or the product is warmed to 33°C to 37°C, it must be used within 12 hours.

Thawing at Room Temperature (not above +25°C) followed by Warming in Incubator (possibility of interim storage for up to 14 days at temperatures not exceeding +25°C):
Maintain the pre-filled syringe in pouches and thaw at room temperature outside the sterile field (See Table 3 for minimum thawing/warming times). Warm the pre-filled syringe, packed in both pouches, in an incubator at 33°C to 37°C outside the sterile field. After thawing/warming in the incubator, remove the outer pouch and transfer the pre-filled syringe, inside the inner pouch, into the sterile field.

Table 3: Thawing at Room Temperature and Warming in Incubator
Pack Size | Thawing at Room Temperature (Not above +25°C) | Warming in Incubator (33°C to 37°C)
2 mL | 80 minutes | 11 minutes
4 mL | 90 minutes | 13 minutes
10 mL | 160 minutes | 25 minutes

The Sealer Protein and the Thrombin solutions should be clear or slightly opalescent. Do not use solutions that are cloudy, discolored, have deposits, or other changes in their appearance. If one of the above occurs, dispose of the solutions.

The thawed Sealer Protein solution should be liquid but slightly viscous. If the solution has the consistency of a solidified gel, do NOT use ARTISS.

2.3 Method of Application

ARTISS must be applied only to application sites that are visible. Individualize the amount to be applied based on the size of the surface to be covered. Prior to applying ARTISS, dry the site of application using standard techniques (e.g., intermittent application of compresses, swabs, use of suction devices). Do not use pressurized air or gas for drying the site. Apply ARTISS as a thin layer.

Application with Spray Device

Ensure that parts of the body outside the desired application area are sufficiently covered to prevent tissue adherence at undesired site.

By slowly pressing on the back of the plunger, apply as a thin layer to avoid the formation of excess granulation tissue and to ensure gradual absorption of the polymerized fibrin sealant. Excessive clot thickness may delay the natural wound healing process. Ensure that the amount applied is sufficient to entirely cover the intended application area.

Attach the skin flap or graft to the wound bed immediately after ARTISS has been sprayed. Wet gloves with normal saline before product contact to prevent adherence. The surgeon has up to 60 seconds to manipulate and position the flap or graft prior to polymerization.

Repeat application, if necessary, to any small areas that may not have been previously treated.

Hold the flap or graft in the desired position by gentle compression for at least 3 minutes to ensure ARTISS sets properly and firmly adheres the skin graft or flap to the underlying tissue. The solidified fibrin sealant reaches its final strength in approximately 2 hours after application.

When applying ARTISS using a spray device, utilize the recommended gas, pressure and distance from tissue within the ranges recommended by the manufacturer as follows:

Table 4: Recommended pressure, distance, and devices for spray application of ARTISS
Surgery | Spray Set/Applicator tips to use | Pressure regulator to use | Gas | Recommended Distance from target tissue | Recommended Spray Pressure
Open wound surgery of subcutaneous tissue | Artiss Spray Set 1 and 10 pack | EASYSPRAY | Medical grade CO2 [Medical grade CO2 is the preferred gas for application, however Compressed Air or Nitrogen are acceptable gasses for administration of ARTISS in open surgery.] , Compressed Air or Nitrogen | 10-15 cm | 1.5-2.0 bar (21.8-29.0 psi)

Apply using the EASYSPRAY and Spray Set, or an equivalent device cleared by FDA for application of ARTISS. See additional instructions for use provided with the EASYSPRAY and Spray Set. ARTISS must not be used with the EASYSPRAY and Spray Set system in enclosed body cavities.

The aerosolized sealant should be applied to the wound in a painting motion from side to side to achieve an even thin layer. The wound bed will glisten in the area to which fibrin sealant has been applied. Any areas not covered by fibrin sealant will be clearly visible. When using accessory tips with this product, the instructions for the use of the tips should be followed.

Application with DUPLOJECT COMBI

The cannulas included with the DUPLOJECT COMBI may be used for small wounds or for edges of a skin graft that did not adhere to the wound bed [see Warnings and Precautions (5)]. Immediately before application, expel and discard the first several drops from the application cannula to ensure adequate mixing of the Sealer Protein and Thrombin solutions in cases where very small volumes (1-2 drops) are administered.

DUPLOJECT COMBI Instructions (see Figure 1)

1. Expel all air from the syringe prior to attaching any application device.
2. Align the joining piece and tether to the side of the syringe with the tether strap hole.
3. Connect the nozzles of the double chamber ready-to-use syringe to the joining piece, ensuring that they are firmly attached.
4. Secure the joining piece by fastening the tether strap to the double chamber ready-to-use syringe.
5. If the tether strap tears, use the spare joining piece provided in the kit. If a spare joining piece is not available, the system can still be used if care is taken to ensure that the connection is secure and leak-proof.
6. Do NOT expel the air remaining inside the joining piece.
7. Attach an application cannula on to the joining piece.
8. Do NOT expel the air remaining inside the joining piece and inside the application cannula until the start of the actual application because this may clog the application cannula.

Note: Interruption of application causes clogging in the cannula. Replace the cannula immediately prior to resuming application. If the opening of the joining piece (Y connector) facing the cannula is clogged, use the spare joining piece provided in the package.

Figure 1: DUPLOJECT COMBI

Pre-filled syringes are for single-patient-use only. Discard unused contents.

When using application devices cleared by FDA for use with ARTISS, strictly follow the Instruction for Use of the device.

3 DOSAGE FORMS AND STRENGTHS

ARTISS is a two-component fibrin sealant solution, comprised of Sealer Protein (Human) and Thrombin (Human) available in a 2 mL, 4 mL, or 10 mL (total volume) pre-filled syringe with the DUPLOJECT COMBI.

4 CONTRAINDICATIONS

ARTISS is contraindicated for the following:

- Intravascular Application: Do not inject directly into the circulatory system or into highly vascularized tissue. Intravascular application can result in life-threatening thromboembolic events and can increase the likelihood and severity of acute hypersensitivity reaction in susceptible patients.
- Aprotinin Hypersensitivity: Do not use in individuals with a known hypersensitivity to aprotinin and/or hypersensitivity to any of the active substances or excipients of ARTISS including proteins such as fibrinogen, thrombin, and human albumin [see Warnings and Precautions (5.1) and Adverse Reactions (6)].
- Application below the minimum recommended distance from the target site: Do not spray where the minimum recommended distance from the applicator tip to the target site cannot be assured.

5 WARNINGS AND PRECAUTIONS

5.1 Hypersensitivity Reactions

Hypersensitivity reactions, including anaphylaxis, can occur. Cases have been reported in post-marketing experience with fibrin sealant. In specific cases, these reactions have progressed to anaphylaxis. Such reactions may especially be seen if product is applied repeatedly over time or in the same setting, or if systemic aprotinin has been administered previously; however, these reactions may also occur in patients receiving ARTISS for the first time. A first successful treatment does not exclude a later allergic reaction. Symptoms associated with allergic anaphylactic reactions include: Flushing urticaria, pruritus, nausea, drop in blood pressure, tachycardia or bradycardia, dyspnea, severe hypotension and anaphylactic shock.

Aprotinin, a monomeric polypeptide, is known to be associated with anaphylactic reactions. Even in the case of strict local application of aprotinin, there is a risk of anaphylactic reactions to aprotinin, particularly in the case of previous exposure [see Contraindications (4)].
Discontinue administration in the event of hypersensitivity reactions. Remove the already applied, polymerized product from the surgical field. Mild reactions can be managed with antihistamines. Severe reactions and reactions involving hypotension require immediate resuscitative intervention.

5.2 Air or Gas Embolism

Life threatening/fatal air or gas embolism, tissue rupture or gas entrapment with compression, have occurred with the use of spray devices employing pressure regulator to administer fibrin sealants. This can occur if a spray device is used at higher than recommended pressures and in closer than recommended proximity to the tissue surface. The risk appears to be higher when fibrin sealants are sprayed with air, as compared to CO2 and therefore cannot be excluded with ARTISS when sprayed in open surgical procedures.

To reduce the risk of a potentially life-threatening gas embolism when using a spray device, be sure to use the pressure within the pressure range recommended by the spray device manufacturer. In the absence of a specific recommendation avoid using pressure above 20-25 psi. Do not spray closer than the distance recommended by the spray device manufacturer. In the absence of a specific recommendation avoid spraying closer than 10-15 cm from the surface of the tissue. When spraying, changes in blood pressure, pulse, oxygen saturation and end tidal CO2 should be monitored because of the possibility of occurrence of air or gas embolism. When using the EASYSPRAY device, or an equivalent spray device cleared by FDA, use the pressure within the pressure range recommended by the spray device manufacturer. Spray only on to visible application sites, not in enclosed body cavities.

5.3 Protein Denaturation

Solutions containing alcohol, iodine or heavy metals may interfere with the product’s performance due to denaturation of proteins or other mechanisms. If any of these substances have been used to clean the wound area, the area should be thoroughly rinsed and dried before application of ARTISS.

5.4 Transmission of Infectious Agents

ARTISS is made from human plasma and therefore, it may carry a risk of transmitting infectious agents, e.g., viruses, the variant Creutzfeldt-Jakob disease (vCJD) agent, and theoretically, the Creutzfeldt-Jakob disease (CJD) agent. All infections thought possibly to have been transmitted by this product should be reported by the physician or other healthcare provider to Baxter Healthcare Corporation, at 1-888-229-0001.

Some viruses, such as parvovirus B19, are particularly difficult to remove or inactivate at this time. Parvovirus B19 most seriously affects pregnant women (fetal infection), immune-compromised individuals or individuals with an increased erythropoiesis (e.g., hemolytic anemia) [see Pregnancy (8.1) and Patient Counseling Information (17)].

6 ADVERSE REACTIONS

6.1 Clinical Trials Experience

Because clinical trials are conducted under widely varying conditions, adverse reaction rates observed in the clinical trials of a drug cannot be directly compared to rates in the clinical trials of another drug and may not reflect the rates observed in practice.

The safety data described in this section reflects exposure of ARTISS in four clinical trials, Study 1, Study 2, Study 3, and Study 4. A total of 298 patients received ARTISS to adhere autologous skin grafts to surgically prepared wound beds resulting from burns in Study 1 and Study 2 or to adhere tissue flaps during facial rhytidectomy surgery in Study 3 and Study 4. The mean volume of ARTISS applied was 2.63 mL (range 0.2 to 12 mL). The follow up duration for Studies 1 and 2 was 12 months. The follow up duration for studies 3 and 4 was 14 days [see Clinical Studies (14)].

Adverse reactions in the burn trials occurring in greater than 1% of subjects were skin graft failure (3%), hematoma (1%) and pruritus (1%) [n=178].

Adverse reactions in the facial rhytidectomy trials occurring in greater than 1% of subjects were hematoma/seroma (4%) [n=120].

6.2 Post-Marketing Experience

The following adverse reactions have been identified during post-approval of ARTISS. Because these reactions are reported voluntarily from a population of uncertain size, it is not always possible to reliably estimate their frequency or establish a causal relationship to product exposure.

Air embolism [See Application Precautions (5.2)]

7 DRUG INTERACTIONS

Oxycellulose containing preparations may reduce the efficacy of ARTISS and should not be used as carrier materials. No interaction studies have been performed.

8 USE IN SPECIFIC POPULATIONS

8.1 Pregnancy

Risk Summary
There are no available data on ARTISS use in pregnant women to inform a drug-associated risk of adverse developmental outcomes. Animal reproduction studies have not been conducted. It is also not known whether ARTISS can cause fetal harm when administered to a pregnant woman or can affect reproduction capacity. Some viruses, such as parvovirus B19, are particularly difficult to remove or inactivate at this time. Parvovirus B19 most seriously affects pregnant women (fetal infection).

The estimated background risk of major birth defects and miscarriage for the indicated populations are unknown. All pregnancies have a background risk of birth defect, loss, or other adverse outcomes. In the U.S. general population, the estimated background risk of major birth defects and miscarriage in clinically recognized pregnancies is 2-4% and 15-20%, respectively.

8.2 Lactation

Risk Summary
There are no direct or controlled studies of ARTISS in lactating women. It is not known whether this drug is excreted in human milk, there is no information regarding the effects on the breastfed infant, and the effects on milk production.
The developmental and health benefits of breastfeeding should be considered along with the mother’s clinical need for ARTISS and any potential adverse effects on the breastfed child from ARTISS or from underlying maternal condition.

8.4 Pediatric Use

The safety and efficacy of ARTISS have been established in pediatric patients. The use of ARTISS to adhere autologous skin grafts to surgically prepared wound beds resulting from burns was supported by data from two clinical trials (Studies 1 and Study 2) which included 38 pediatric patients between 1 to 16 years of age. The use of ARTISS to adhere tissue flaps during facial rhytidectomy was supported by extrapolation of the data from two clinical studies (Study 3 and Study 4) in adult patients [see Adverse Reactions (6) and Clinical Studies (14)].

8.5 Geriatric Use

Study 3 and Study 4 included 13 patients aged 65 years and older. No overall differences in safety or effectiveness were observed between these subjects and younger subjects.

10 OVERDOSAGE

To avoid the formation of excess granulation tissue and to ensure gradual absorption of the polymerized fibrin sealant, apply only a thin layer [ Dosage and Administration (2.3)].

11 DESCRIPTION

ARTISS [Fibrin Sealant (Human)] is a two-component fibrin sealant made from pooled human plasma.

Sealer Protein Solution
Total protein: 96 -125 mg/mL
Fibrinogen: 67 - 106 mg/mL
Fibrinolysis Inhibitor, Aprotinin (Synthetic): 2250 - 3750 Kallidinogenase Inhibiting Unit/mL

Other ingredients include: Human albumin, tri-sodium citrate, histidine, niacinamide, polysorbate 80 and water for injection (WFI).

Thrombin Solution
Thrombin (Human): 2.5 - 6.5 units/mL^1
Calcium Chloride: 36 - 44 µmol/mL
Other ingredients include: Human albumin, sodium chloride and water for injection (WFI).

^1 The potency expressed in units is determined using a clotting assay against an internal reference standard for potency that has been calibrated against the World Health Organization (WHO) Second International Standard for Thrombin, 01/580. Therefore, a unit is equivalent to an International Unit (IU).

Sealer Protein (Human)

Sealer Protein (Human) is a sterile, non-pyrogenic, vapor-heated and solvent/detergent treated preparation made from pooled human plasma. Sealer Protein (Human) is provided as a frozen liquid solution pre-filled into one side of a dual-chambered syringe (1). The active ingredient in Sealer Protein (Human) is fibrinogen. A Fibrinolysis Inhibitor, Aprotinin (Synthetic) is included in the Sealer Protein (Human) component to delay fibrinolysis. Aprotinin (Synthetic) is manufactured by solid phase synthesis from materials completely of non-human/non-animal origin.

Thrombin (Human)

Thrombin (Human) is a sterile, non-pyrogenic, vapor-heated and solvent/detergent treated preparation made from pooled human plasma. Thrombin (Human) is provided as a frozen liquid solution pre-filled into one side of a dual-chambered syringe (2).

Sealer Protein (Human) and Thrombin (Human) are made from pooled human plasma collected at U.S. licensed collection centers. The vapor heat and solvent/detergent treatment steps used in the manufacturing process have been shown to be capable of significant viral reduction. No procedure, however, has been shown to be completely effective in removing viral infectivity from derivatives of human plasma [see Viral Clearance below and Warnings and Precautions (5.4)].

Viral Clearance

The manufacturing procedure includes processing steps designed to further reduce the risk of viral transmission. In particular, vapor heating and solvent/detergent treatment processes are included in the manufacturing of Sealer Protein and Thrombin. Validation studies were conducted using samples drawn from manufacturing intermediates for each of the two human plasma derived components. These samples were spiked with stock virus suspensions of known titers followed by further processing under conditions equivalent to those in the respective manufacturing steps. The stock virus suspensions represent HIV-1, BVDV, PRV, HAV and MMV (Human Parvovirus B19).
The virus reduction factors (expressed as log10) of independent manufacturing steps are shown in Table 5 for each of the viruses tested:

Table 5: Mean Reduction Factors [log10] for Virus Removal and/or Inactivation

Sealer Protein Component

Manufacturing Step | HIV-1^1 | BVDV^1 | PRV^1 | HAV^2 | MMV^2
Early Manufacturing Steps | n.d. | n.d. | n.d. | n.d. | 2.7
Solvent/Detergent Treatment | ≥4.7 | ≥5.3 | ≥5.5 | n.d. | n.d.
Vapor Heat Treatment | >5.9 | >6.5 | >6.8 | >6.2 | 1.4
Overall Reduction Factor (ORF) | >10.6 | >11.8 | ≥12.3 | >6.2 | 4.1

Thrombin Component

Manufacturing Step | HIV-1^1 | BVDV^1 | PRV^1 | HAV^2 | MMV^2
Thrombin Precursor Mass Capture | 3.2 | 1.8 | 2.5 | 1.5 | 1.2
Vapor Heat Treatment | >5.3 | >5.9 | >6.8 | >4.6 | 1.0
Solvent/Detergent Treatment | ≥5.3 | ≥5.3 | ≥6.2 | n.d. | n.d.
Ion Exchange Chromatography | n.d. | n.d. | n.d. | n.d. | 3.6
Overall Reduction Factor (ORF) | >13.8 | >13.0 | >15.5 | >6.1 | 5.8

In addition, Human Parvovirus B19 was used to investigate the upstream Thrombin precursor mass capture step, the Sealer Protein early manufacturing steps and the Thrombin and Sealer Protein vapor heating steps. Using quantitative PCR assays, the estimated log reduction factors obtained were 1.7 and 3.4 for the Thrombin precursor mass capture step and Sealer Protein early manufacturing steps and >4 / 1.0 for the Thrombin / Sealer Protein vapor heating steps, respectively.

12 CLINICAL PHARMACOLOGY

12.1 Mechanism of Action

Upon mixing Sealer Protein (Human) and Thrombin (Human), the two components mimic the final stage of the blood coagulation cascade. Soluble fibrinogen is transformed into fibrin that adheres to the wound surface and to the skin flap or graft to be affixed. Due to the low thrombin concentration, initial polymerization will take up to 60 seconds. The fibrin clot continues to strengthen for up to 2 hours after application.

Spray application over the wound bed provides full surface adherence of skin flaps and grafts. Full surface adherence minimizes areas of dead space between the wound bed and applied tissues. Elimination of dead space prevents shear irritation upon movement as well as reduces the void space under the skin that can host fluid build-up.

12.2 Pharmacodynamics

Thrombin is a highly specific protease that transforms the fibrinogen contained in Sealer Protein (Human) into fibrin.

Fibrinolysis Inhibitor, Aprotinin (Synthetic), is a polyvalent protease inhibitor that prevents premature degradation of fibrin. Free Aprotinin and its metabolites have a half-life of 30 to 60 minutes and are eliminated by the kidney. Preclinical studies with different fibrin sealant preparations simulating the fibrinolytic activity generated by extracorporeal circulation in patients during cardiovascular surgery have shown that incorporation of aprotinin in the product formulation increases resistance of the fibrin sealant clot to degradation in a fibrinolytic environment.

14 CLINICAL STUDIES

The efficacy of ARTISS was evaluated in four clinical studies, Study 1 (NCT00161759), Study 2 (NCT00157131), Study 3 (NCT00708071), and Study 4 (NCT00999141), as described below.

Study 1 Burns (grafts)
The safety and efficacy of ARTISS compared to staples for wound healing through surgical closure was investigated in 40 patients in a multicenter, prospective, randomized, comparative feasibility study.
The primary objective was to compare ARTISS to the current standard of care (staples) when used to adhere autologous skin grafts to surgically prepared wound beds resulting from burns.

The mean (SD) volume of ARTISS applied was 2.9 (1.64) mL. Postoperative follow-up was planned for one year, with an initial 3-month assessment period, followed by long-term cosmetic evaluations up to 12 months.

The population demographics include: mean age was 31 years (range: 6 to 55 years), 29 patients (73%) were male.

The adherence of skin grafts on ARTISS -treated sites was rated as excellent or good in 97.5% of the 40 subjects treated on Day 0.
The median percent area of hematoma and seroma formation on Day 1 was significantly lower for ARTISS-treated sites (0.0%) compared to stapled sites (2.1%) (p = 0.0138).
Investigators reported similar clinical impressions of pigmentation, vascularization, and pliability for both treatments, with normal pigmentation observed in a comparable proportion of subjects over time.
No statistically significant differences were found between ARTISS-treated sites and stapled sites regarding keloid formation and hypertrophic scarring at the 6, 9, or 12-month evaluations.
Wound closure by Day 28 was achieved in 79.5% of ARTISS-treated sites and 59.0% of the stapled test sites, a statistically significant difference (p = 0.0215).

Study 2 Burns (grafts)
ARTISS was investigated for adherence of split thickness sheet skin grafts in burn patients in a prospective, randomized, controlled, evaluator-blinded, multicenter clinical trials. In each of the 138 patients, two comparable test sites were identified after burn wound excision. Skin grafts were adhered at one test site using ARTISS, and at the other test site using staples (control). The study product was applied once to the wound bed of the allocated test site during skin grafting surgery. The mean (SD) volume of ARTISS applied was 2.9 (1.9) mL.

The population demographics include: mean age was 31 years (range: 1 to 63 years), 94 patients (68%) were male.

The mean ± standard deviation (SD) estimated total body surface area (TBSA) for all burn wounds was 13.6 ± 9.2%. The mean ± SD estimated TBSA requiring skin grafting was 8.0 ± 6.9%. The mean ± SD estimated TBSA for ARTISS test sites was 1.7 ± 0.8% and for the stapled test sites was 1.7 ± 0.7%. Burn wound thickness was classified as full thickness in 106 (76.8%) of the 138 treated subjects, and partial thickness in 32 (23.2%) subjects.

The safety population contained all 138 treated subjects; however, 11 subjects did not have an available primary endpoint assessment, leaving a modified intent-to-treat (ITT) set of 127 patients. Complete wound closure by Day 28 was achieved in 43.3% of the ARTISS test sites and 37.0% of the stapled test sites in the 127 ITT patients. Wound closure at Day 28 was complete at 72% of the ARTISS and staples test sites for the 1-6 years old group (N=18), at 32% of the ARTISS test sites and 26% of the staples test sites for the 7-18 years old group (N=19) and at 40% of the ARTISS test sites and 32% of the staples test sites for the greater then 18 years old group [ITT]. The lower limit of the 97.5% confidence interval of the difference between ARTISS and staples was -0.029. A similar result was obtained in the per protocol (PP) population: complete wound closure by Day 28 was achieved in 45.3% of the ARTISS test sites and 39.6% of the stapled test sites in the 106 PP patients. The lower limit of the 97.5% confidence interval of the difference between ARTISS and staples was -0.041. Therefore, ARTISS was found to be non-inferior to staples in the ITT and PP populations at the 97.5% one-sided level for complete wound closure by Day 28 because the lower limit of the confidence interval of the difference between ARTISS and staples success rates was greater than the predefined limit of -0.1.

Study 3 and Study 4 Facial Rhytidectomy (flaps)

ARTISS was investigated for adherence of skin flaps in facial rhytidectomy surgeries during two prospective, randomized, controlled, multicenter clinical trials. Both Study 3, investigating 45 subjects and Study 4, with 75 subjects had a split-face design in which 1 side of the face was treated with ARTISS as an adjunct to the standard of care (SoC) and the other side received SoC only, which was closure of the flap by means of staples and suturing only; therefore each subject participated in both arms (ARTISS and SoC).

For both studies, the primary endpoint was the total drainage volume collected from each side of the face at 24 h (±4 h) post surgery. The secondary endpoints were occurrence of hematoma and seroma on each side of the face, comparison of edema between the 2 sides of the face, changes in skin sensitivity from baseline on each side of the face and subject preference.

In both studies, a standardized drain was placed in each side of the face prior to the flap closure and drainage volume from both sides of the face from all subjects was compared. Pressure dressings were not allowed.

The population demographics include: For Study 3, mean age was 55 years (range: 43 to 70 years) and 42 patients (93%) were female. For Study 4, mean age was 54 years (range: 40 to 71 years) and 71 patients (95%) were female.

The results for the primary endpoint are presented in Table 6 below.

Table 6: Drainage Volume Comparison at 24 h Post Operative
Clinical Trial | Mean ± SD Drainage (mL) ARTISS Side of the Face | Mean ± SD Drainage (mL) SoC Side of the Face | p-Value
Study 3 | 11.5 ± 13.7 | 26.8 ± 24.0 | < 0.0001
Study 4 | 7.7 ± 7.4 | 20.0 ± 11.3 | <0.0001

A statistically significant difference in drainage volumes was observed, favoring the side of the face treated with ARTISS.

An integrated analysis of the occurrence of hematoma/seroma in all 120 subjects across the two studies was performed. A comparison of the proportion of subjects experiencing a hematoma/seroma exclusively on the ARTISS-treated side or on the SoC side of the face is presented in Table 7 below.

Table 7: Occurrence of Hematoma/Seroma
Clinical Trial | ARTISS n (%) | SoC n (%) | Both Sides of Face n (%) | Total n (%)
Study 3 | 0 | 9 (20%) | 0 | 9 (20%)
Study 4 | 2 (2.7%) | 5 (6.7%) | 3 (4%) | 10 (13.3%)

16 HOW SUPPLIED/STORAGE AND HANDLING

Table 8: NDC Numbers
Pack Size | Packaging Component | NDC
2 mL | Carton | 0338-9637-01
4 mL | Carton | 0338-9639-01
10 mL | Carton | 0338-9641-01

Storage

Store in original carton to protect from light. Do not use after the expiration date stated on the carton and the pouch label. Discard if packaging of any component is damaged.

- Store frozen (at ≤ -20°C) until preparation for use.
- After thawing and warming at 33°C-37°C, the product must be used within 12 hours.
- After thawing at room temperature, the product can be stored for up to 14 days at temperatures not exceeding 25°C, provided it remains sealed in the original packaging (both pouches).
- Do not refrigerate or re-freeze after thawing. Do not microwave

17 PATIENT COUNSELING INFORMATION

Discuss following with the patient and/or caregivers:

- Hypersensitivity Reactions: Inform the patient and/or caregivers that hypersensitivity reactions may occur with ARTISS and advise to seek immediate medical evaluation if any signs and symptoms of hypersensitivity occur. These may include: flushing urticaria, pruritus, nausea, drop in blood pressure, tachycardia or bradycardia, dyspnea, severe hypotension and anaphylactic shock.
- Transmission of infectious agents: Inform the patient and/or caregivers that ARTISS is made from human plasma and it may carry a risk of transmitting infectious agents [see Warning and Precautions (5)], e.g., viruses, the variant Creutzfeldt-Jakob disease (vCJD) agent, and theoretically, the Creutzfeldt-Jakob disease (CJD) agent. Parvovirus B19 infection may be serious for pregnant women (fetal infection) and for individuals with immunodeficiency or increased red blood cell turnover. Instruct patients to consult their physician if symptoms of B19 virus infection appear (fever, drowsiness, chills and runny nose followed about two weeks later by a rash and joint pain) [see Pregnancy (8.1)].

Manufactured For Baxter Healthcare Corporation

Deerfield, IL 60015 USA

US License No. 140

Baxter, Artiss, Duploject, EASYSPRAY and Tisseel are trademarks of Baxter International Inc., or its subsidiaries.

PACKAGE/LABEL PRINCIPAL DISPLAY PANEL

Pouch Label

Fibrin Sealant (Human)
ARTISS 2 mL
NDC 0338-9637-01
Frozen

Baxter Logo

Temperature sensitive – Do NOT expose above 37°C (99°F).

Contents:

Pre-filled syringe containing:
– Sealer Protein Solution ➊: 1 mL, sterile
– Fibrinogen (Human), 86.5 mg/mL
– Fibrinolysis Inhibitor (Aprotinin,
Synthetic), 3000 KIU/mL
– Thrombin Solution ➋: 1 mL, sterile
– Thrombin (Human), 4 units/mL
– Calcium Chloride, 40 μmol/mL

TOPICAL USE ONLY
DO NOT INJECT
Read directions for thawing and application before use.
Store at –20°C (–4°F) or colder. Unopened pouches,
thawed at room temperature, may be stored for up to
14 days at 15 – 25°C.
Do not refrigerate, microwave, or re-freeze.
Rx Only
Contents were sterilized and
packaged under aseptic conditions.

Manufactured for Baxter
Healthcare Corporation
Deerfield IL, 60015 USA
U.S. License No. 140
0752951

Barcode

Green triangle symbol

Barcode

Lot No.:

Exp. Date:

Carton Label

Baxter Logo

Artiss 2 mL
Fibrin Sealant (Human)
Vapor Heated, Solvent/Detergent Treated, Frozen

NDC 0338-9637-01
2 mL

TOPICAL USE ONLY
DO NOT INJECT

Manufactured for Baxter Healthcare
Corporation
Deerfield, IL 60015 USA
1-888-229-0001

U.S. License No. 140
Made in Austria

Reorder Number: 5500694

Baxter and Artiss are trademarks of Baxter
International Inc.

GTIN (01) 00303389637011
LOT (10)
EXPIRY (17)
SERIAL (21)

Baxter Logo
2 mL

Barcode

Artiss 2 mL
Fibrin Sealant (Human)
Vapor Heated, Solvent/Detergent Treated, Frozen

Baxter Logo
2 mL

Baxter Logo

NDC 0338-9637-01

Artiss 2 mL
Fibrin Sealant (Human)
Vapor Heated, Solvent/Detergent Treated, Frozen

Contents:
Pre-filled syringe containing:
Sealer Protein Solution: 1 mL, sterile

- Fibrinogen (Human), 86.5 mg/mL
  Vapor Heated, Solvent/Detergent Treated
- Fibrinolysis Inhibitor (Aprotinin, Synthetic), 3000 KIU/mL

Thrombin Solution: 1 mL, sterile

- Thrombin (Human), 4 units/mL
  Vapor Heated, Solvent/Detergent Treated
- Calcium Chloride, 40 μmol/mL

TOPICAL USE ONLY
DO NOT INJECT
Do not use on individuals with a known hypersensitivity
to aprotinin and/or any of the active substances or
excipients.
The risks and benefits of this product should be
discussed with the patient.
Read full prescribing information before use.
Store at –20°C (–4°F) or colder.
Unopened pouches,thawed at room temperature,
may be stored for up to 14 days at 15 – 25°C.
Do not refrigerate, microwave, or re-freeze.
For Single Patient Use Only
No preservative
Not made with natural rubber latex
Rx only

2 mL

Artiss 2 mL
Fibrin Sealant (Human)
Vapor Heated, Solvent/Detergent Treated, Frozen

2 mL

0752952

Artiss 2 mL
Fibrin Sealant (Human)
Vapor Heated, Solvent/Detergent Treated, Frozen

Barcode

NDC 0338-9637-01

Baxter Logo

2 mL

Barcode
N3 0338-9637-01 1

Pouch Label

Fibrin Sealant (Human)
ARTISS 4 mL
NDC 0338-9639-01
Frozen

Baxter Logo

Temperature sensitive – Do NOT expose above 37°C (99°F).

Contents:

Pre-filled syringe containing:
– Sealer Protein Solution ➊: 2 mL, sterile
– Fibrinogen (Human), 86.5 mg/mL
– Fibrinolysis Inhibitor (Aprotinin,
Synthetic), 3000 KIU/mL
– Thrombin Solution ➋: 2 mL, sterile
– Thrombin (Human), 4 units/mL
– Calcium Chloride, 40 μmol/mL

TOPICAL USE ONLY
DO NOT INJECT
Read directions for thawing and application before use.
Store at –20°C (–4°F) or colder. Unopened pouches,
thawed at room temperature, may be stored for up to
14 days at 15 – 25°C.
Do not refrigerate, microwave, or re-freeze.
Rx Only
Contents were sterilized and
packaged under aseptic conditions.

Manufactured for Baxter
Healthcare Corporation
Deerfield IL, 60015 USA
U.S. License No. 140
0752955

Barcode

Red triangle symbol

Barcode

Lot No.:

Exp. Date:

Carton Label

Baxter Logo

Artiss 4 mL
Fibrin Sealant (Human)
Vapor Heated, Solvent/Detergent Treated, Frozen

NDC 0338-9639-01
4 mL

TOPICAL USE ONLY
DO NOT INJECT

Manufactured for Baxter Healthcare
Corporation
Deerfield, IL 60015 USA
1-888-229-0001

U.S. License No. 140
Made in Austria

Reorder Number: 5500695

Baxter and Artiss are trademarks of Baxter
International Inc.

GTIN (01) 00303389639015
LOT (10)
EXPIRY (17)
SERIAL (21)

Baxter Logo
4 mL

Barcode

Artiss 4 mL
Fibrin Sealant (Human)
Vapor Heated, Solvent/Detergent Treated, Frozen

Baxter Logo
4 mL

Baxter Logo

NDC 0338-9639-01

Artiss 4 mL
Fibrin Sealant (Human)
Vapor Heated, Solvent/Detergent Treated, Frozen

Contents:
Pre-filled syringe containing:
Sealer Protein Solution: 2 mL, sterile

- Fibrinogen (Human), 86.5 mg/mL
  Vapor Heated, Solvent/Detergent Treated
- Fibrinolysis Inhibitor (Aprotinin, Synthetic), 3000 KIU/mL

Thrombin Solution: 2 mL, sterile

- Thrombin (Human), 4 units/mL
  Vapor Heated, Solvent/Detergent Treated
- Calcium Chloride, 40 μmol/mL

TOPICAL USE ONLY
DO NOT INJECT
Do not use on individuals with a known hypersensitivity
to aprotinin and/or any of the active substances or
excipients.
The risks and benefits of this product should be
discussed with the patient.
Read full prescribing information before use.
Store at –20°C (–4°F) or colder.
Unopened pouches,thawed at room temperature,
may be stored for up to 14 days at 15 – 25°C.
Do not refrigerate, microwave, or re-freeze.
For Single Patient Use Only
No preservative
Not made with natural rubber latex
Rx only

4 mL

Artiss 4 mL
Fibrin Sealant (Human)
Vapor Heated, Solvent/Detergent Treated, Frozen

4 mL

0752956

Artiss 4 mL
Fibrin Sealant (Human)
Vapor Heated, Solvent/Detergent Treated, Frozen

Barcode

NDC 0338-9639-01

Baxter Logo

4 mL

Barcode
N3 0338-9639-01 5

Pouch Label

Fibrin Sealant (Human)
ARTISS 10 mL
NDC 0338-9641-01
Frozen

Baxter Logo

Temperature sensitive – Do NOT expose above 37°C (99°F).

Contents:

Pre-filled syringe containing:
– Sealer Protein Solution ➊: 5 mL, sterile
– Fibrinogen (Human), 86.5 mg/mL
– Fibrinolysis Inhibitor (Aprotinin,
Synthetic), 3000 KIU/mL
– Thrombin Solution ➋: 5 mL, sterile
– Thrombin (Human), 4 units/mL
– Calcium Chloride, 40 μmol/mL

TOPICAL USE ONLY
DO NOT INJECT
Read directions for thawing and application before use.
Store at –20°C (–4°F) or colder. Unopened pouches,
thawed at room temperature, may be stored for up to
14 days at 15 – 25°C.
Do not refrigerate, microwave, or re-freeze.
Rx Only
Contents were sterilized and
packaged under aseptic conditions.

Manufactured for Baxter
Healthcare Corporation
Deerfield IL, 60015 USA
U.S. License No. 140
0752959

Barcode

Blue triangle symbol

Barcode

Lot No.:

Exp. Date:

Carton Label

Baxter Logo

Artiss 10 mL
Fibrin Sealant (Human)
Vapor Heated, Solvent/Detergent Treated, Frozen

NDC 0338-9641-01
10 mL

TOPICAL USE ONLY
DO NOT INJECT

Manufactured for Baxter Healthcare
Corporation
Deerfield, IL 60015 USA
1-888-229-0001

U.S. License No. 140
Made in Austria

Reorder Number: 5500696

Baxter and Artiss are trademarks of Baxter
International Inc.

GTIN (01) 00303389641018
LOT (10)
EXPIRY (17)
SERIAL (21)

Baxter Logo
10 mL

Barcode

Artiss 10 mL
Fibrin Sealant (Human)
Vapor Heated, Solvent/Detergent Treated, Frozen

Baxter Logo
10 mL

Baxter Logo

NDC 0338-9641-01

Artiss 10 mL
Fibrin Sealant (Human)
Vapor Heated, Solvent/Detergent Treated, Frozen

Contents:
Pre-filled syringe containing:
Sealer Protein Solution: 5 mL, sterile

- Fibrinogen (Human), 86.5 mg/mL
  Vapor Heated, Solvent/Detergent Treated
- Fibrinolysis Inhibitor (Aprotinin, Synthetic),
  3000 KIU/mL

Thrombin Solution: 5 mL, sterile

- Thrombin (Human), 4 units/mL
  Vapor Heated, Solvent/Detergent Treated
- Calcium Chloride, 40 μmol/mL

TOPICAL USE ONLY
DO NOT INJECT
Do not use on individuals with a known hypersensitivity
to aprotinin and/or any of the active substances or
excipients.
The risks and benefits of this product should be
discussed with the patient.
Read full prescribing information before use.
Store at –20°C (–4°F) or colder.
Unopened pouches,thawed at room temperature,
may be stored for up to 14 days at 15 – 25°C.
Do not refrigerate, microwave, or re-freeze.
For Single Patient Use Only
No preservative
Not made with natural rubber latex
Rx only

10 mL

Artiss 10 mL
Fibrin Sealant (Human)
Vapor Heated, Solvent/Detergent Treated, Frozen

10 mL

0752960

Artiss 10 mL
Fibrin Sealant (Human)
Vapor Heated, Solvent/Detergent Treated, Frozen

Barcode

NDC 0338-9641-01

Baxter Logo

10 mL

Barcode
N3 0338-9641-01 8

Duploject Combi Label

Baxter Logo

DUPLOJECT COMBI

Indication for Use:
For the application of TISSEEL and ARTISS Fibrin Sealant.

REF Symbol

Batch code
Use-by date

For single use only. Not made with natural rubber latex.
Do not reuse or resterilize. Sterilize using ethylene oxide.
Sterile and non-pyrogenic in unopened and undamaged package. Rx Only.

Manufactured for:
Baxter Healthcare Corporation
One Baxter Parkway
Deerfield, IL 60015 USA
1-888-229-0001

Made in Belgium

BE-90-01-057